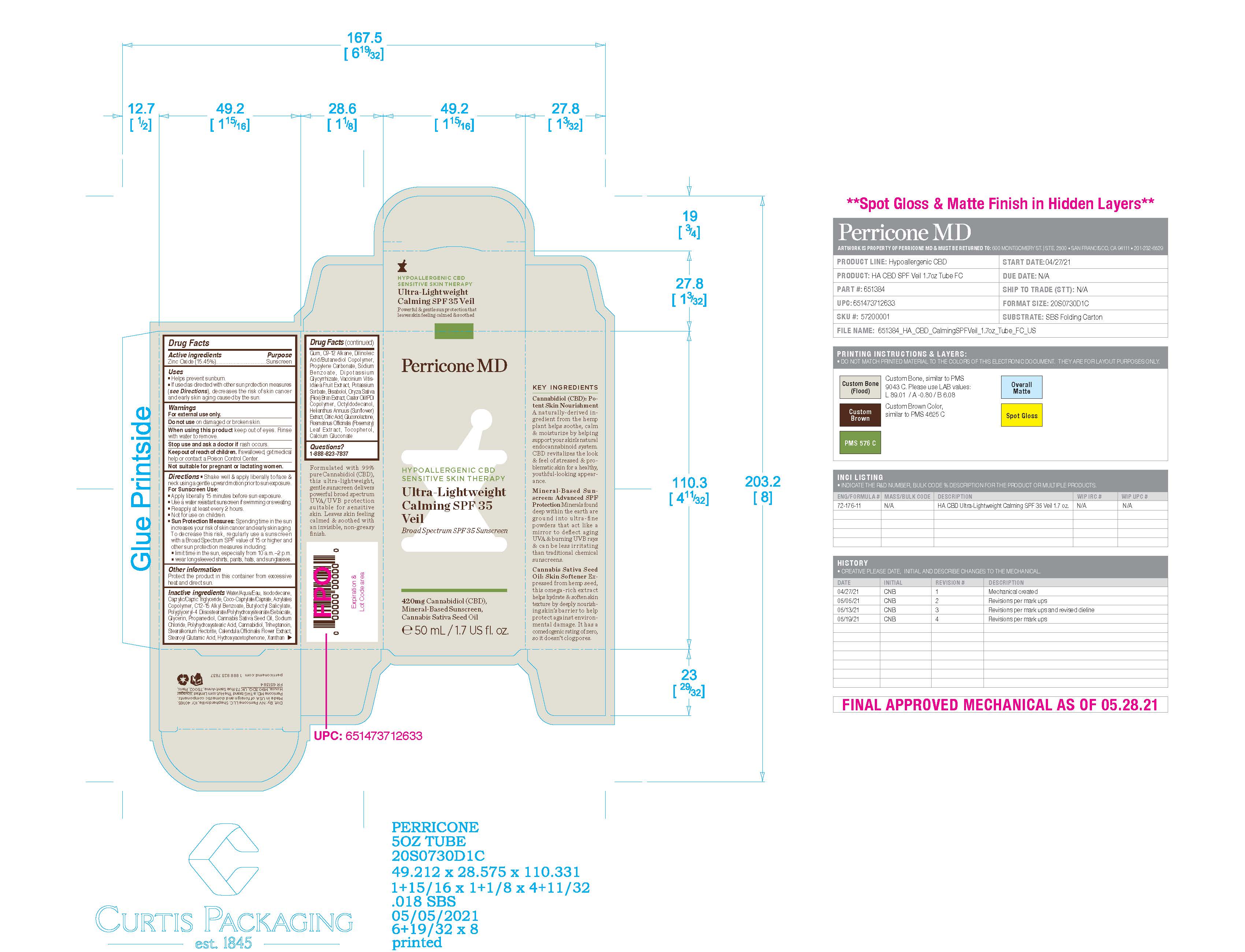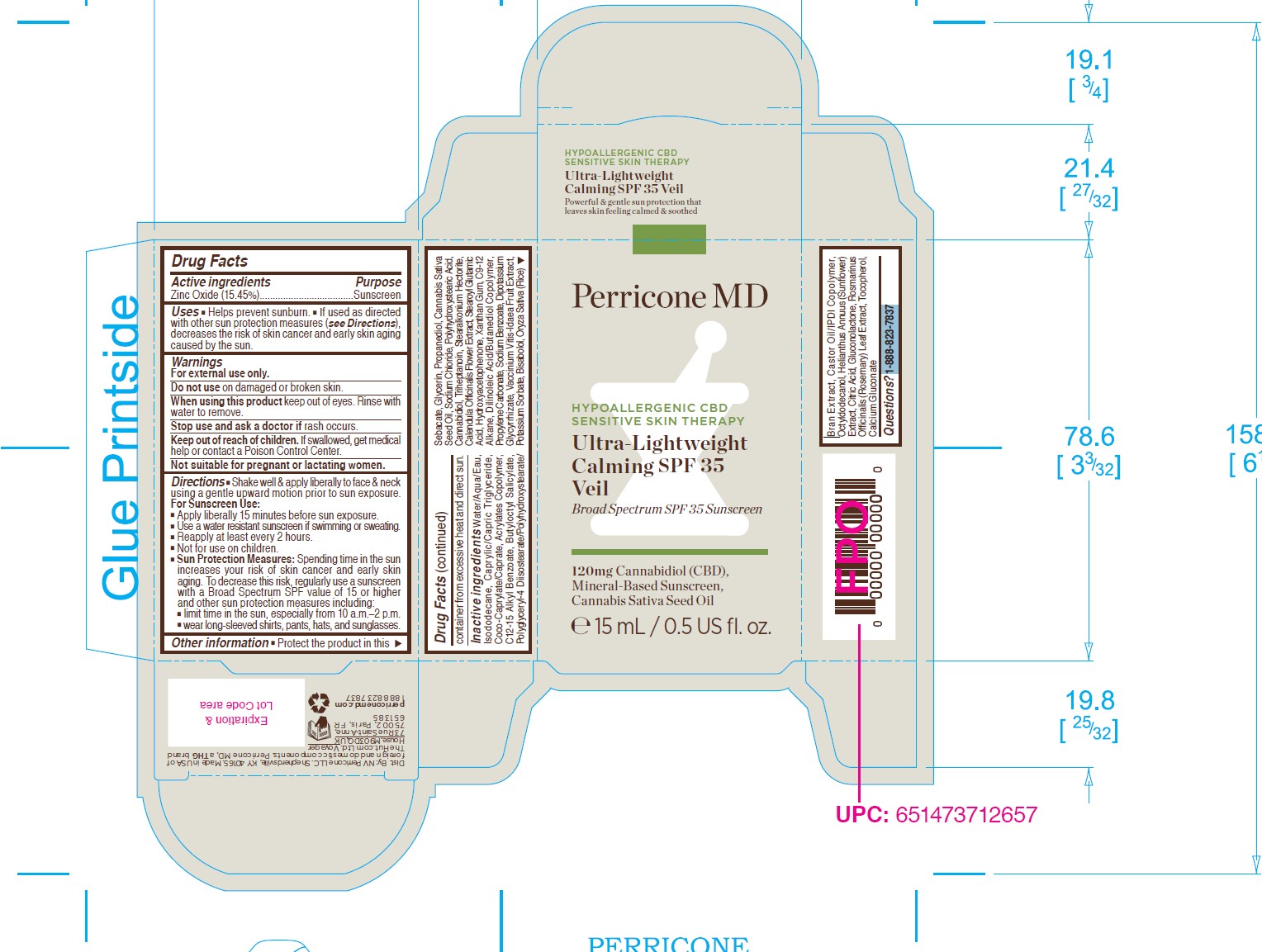 DRUG LABEL: Perricone MD Hypoallergenic CBD Sensitive Skin Therapy Ultra-Lightweight Calming SPF 35 Veil
NDC: 84448-615 | Form: CREAM
Manufacturer: THG Beauty USA LLC
Category: otc | Type: HUMAN OTC DRUG LABEL
Date: 20251103

ACTIVE INGREDIENTS: ZINC OXIDE 15.45 g/100 mL
INACTIVE INGREDIENTS: SODIUM CHLORIDE; GLYCERIN; PROPANEDIOL; LEVOMENOL; STEAROYL GLUTAMIC ACID; POTASSIUM SORBATE; GLUCONOLACTONE; ROSEMARY; WATER; COCO-CAPRYLATE/CAPRATE; POLYGLYCERYL-4 DIISOSTEARATE/POLYHYDROXYSTEARATE/SEBACATE; CALENDULA OFFICINALIS FLOWER; PROPYLENE CARBONATE; CITRIC ACID MONOHYDRATE; TOCOPHEROL; ALKYL (C12-15) BENZOATE; GLYCYRRHIZINATE DIPOTASSIUM; STEARALKONIUM HECTORITE; SUNFLOWER OIL; BUTYLOCTYL SALICYLATE; CANNABIDIOL; XANTHAN GUM; LINGONBERRY; CANNABIS SATIVA SEED OIL; C9-12 ALKANE; SODIUM BENZOATE; ISODODECANE; OCTYLDODECANOL; RICE BRAN; CASTOR OIL/IPDI COPOLYMER; CALCIUM GLUCONATE; DILINOLEIC ACID/BUTANEDIOL COPOLYMER; POLYHYDROXYSTEARIC ACID (2300 MW); HYDROXYACETOPHENONE; MEDIUM-CHAIN TRIGLYCERIDES; BUTYL ACRYLATE/METHYL METHACRYLATE/METHACRYLIC ACID COPOLYMER (18000 MW); TRIHEPTANOIN

ACTIVE INGREDIENT

- Zinc Oxide 15.45

PURPOSE

- Sunscreen

INDICATIONS AND USAGE

- Helps prevent sunburn.
- If used as directed with other sun protection measures (see Directions), decreases the risk of skin cancer and early skin aging caused by the sun.

WARNINGS

- For external use only.

STOP USE

- if rash occurs.

DO NOT USE

- on damaged or broken skin.

WHEN USING

- keep out of eyes. Rinse with water to remove

KEEP OUT OF REACH OF CHILDREN

- If swallowed, get medical help or contact a Poison Control Center.

PREGNANCY OR BREAST FEEDING

- Not suitable for pregnant or lactating women.

DOSAGE AND ADMINISTRATION

- Shake well & apply liberally to face & neck using a gentle upward motion prior to sun exposure.

For Sunscreen Use:

- Apply liberally 15 minutes before sun exposure.
- Use a water resistant sunscreen if swimming or sweating.
- Reapply at least every 2 hours.
- Not for use on children.

Sun Protection Measures:

- Spending time in the sun increases your risk of skin cancer and early skin aging. To decrease this risk, regularly use a sunscreen

with a Broad Spectrum SPF value of 15 or higher and other sun protection measures including:

- limit time in the sun, especially from 10 a.m.–2 p.m.
- wear long-sleeved shirts, pants, hats, and sunglasses.

OTHER SAFETY INFORMATION

- Protect the product in this container from excessive heat and direct sun.

INACTIVE INGREDIENT

Water/Aqua/Eau, Isododecane, Caprylic/Capric Triglyceride, Coco-Caprylate/Caprate, Acrylates Copolymer, C12-15 Alkyl Benzoate, Butyloctyl Salicylate, Polyglyceryl-4 Diisostearate/Polyhydroxystearate/Sebacate, Glycerin, Propanediol, Cannabis Sativa Seed Oil, Sodium Chloride, Polyhydroxystearic Acid, Cannabidiol, Triheptanoin, Stearalkonium Hectorite, Calendula Officinalis Flower Extract, Stearoyl Glutamic Acid, Hydroxyacetophenone, Xanthan Gum, C9-12 Alkane, Dilinoleic Acid/Butanediol Copolymer, Propylene Carbonate, Sodium Benzoate, Dipotassium Glycyrrhizate, Vaccinium Vitis-Idaea Fruit Extract, Potassium Sorbate, Bisabolol, Oryza Sativa (Rice) Bran Extract, Castor Oil/IPDI Copolymer, Octyldodecanol, Helianthus Annuus (Sunflower) Extract, Citric Acid, Gluconolactone, Rosmarinus Officinalis (Rosemary) Leaf Extract, Tocopherol, Calcium Gluconate

QUESTIONS

- 1-888-823-7837